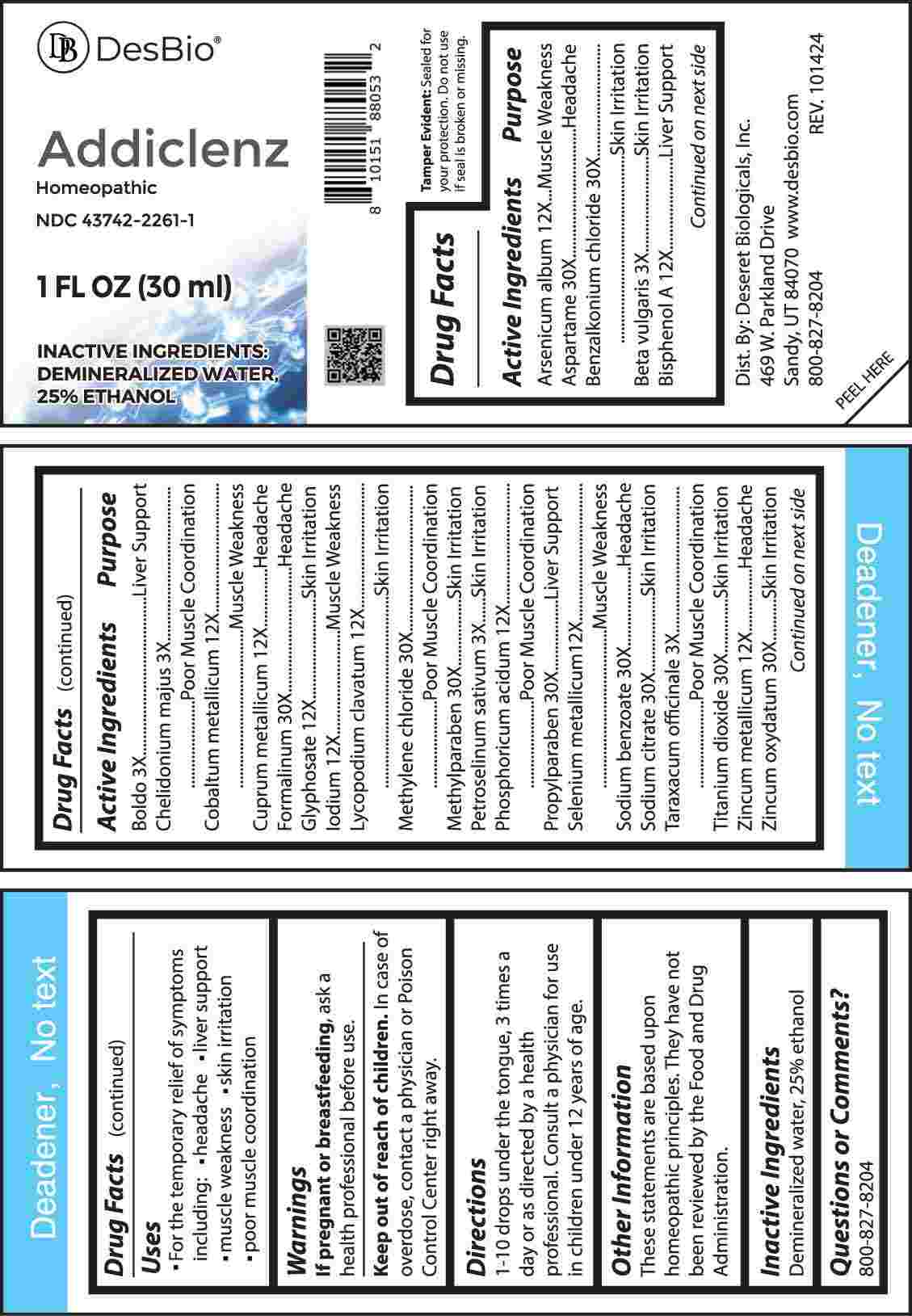 DRUG LABEL: Addiclenz
NDC: 43742-2261 | Form: LIQUID
Manufacturer: Deseret Biologicals, Inc.
Category: homeopathic | Type: HUMAN OTC DRUG LABEL
Date: 20250311

ACTIVE INGREDIENTS: ASPARTAME 30 [hp_X]/1 mL; BENZALKONIUM CHLORIDE 30 [hp_X]/1 mL; FORMALDEHYDE SOLUTION 30 [hp_X]/1 mL; METHYLENE CHLORIDE 30 [hp_X]/1 mL; METHYLPARABEN 30 [hp_X]/1 mL; PROPYLPARABEN 30 [hp_X]/1 mL; SODIUM BENZOATE 30 [hp_X]/1 mL; SODIUM CITRATE, UNSPECIFIED FORM 30 [hp_X]/1 mL; TITANIUM DIOXIDE 30 [hp_X]/1 mL; ZINC OXIDE 30 [hp_X]/1 mL; ARSENIC TRIOXIDE 12 [hp_X]/1 mL; BETA VULGARIS WHOLE 3 [hp_X]/1 mL; BISPHENOL A 12 [hp_X]/1 mL; PEUMUS BOLDUS LEAF 3 [hp_X]/1 mL; CHELIDONIUM MAJUS WHOLE 3 [hp_X]/1 mL; COBALT 12 [hp_X]/1 mL; COPPER 12 [hp_X]/1 mL; GLYPHOSATE 12 [hp_X]/1 mL; IODINE 12 [hp_X]/1 mL; LYCOPODIUM CLAVATUM SPORE 12 [hp_X]/1 mL; PETROSELINUM CRISPUM WHOLE 3 [hp_X]/1 mL; PHOSPHORIC ACID 12 [hp_X]/1 mL; SELENIUM 12 [hp_X]/1 mL; TARAXACUM OFFICINALE 3 [hp_X]/1 mL; ZINC 12 [hp_X]/1 mL
INACTIVE INGREDIENTS: WATER; ALCOHOL

DRUG FACTS:

ACTIVE INGREDIENTS:

Arsenicum Album 12X, Aspartame 30X, Benzalkonium Chloride 30X, Beta Vulgaris 3X, Bisphenol A 12X, Boldo 3X, Chelidonium Majus 3X, Cobaltum Metallicum 12X, Cuprum Metallicum 12X, Formalinum 30X, Glyphosate 12X, Iodium 12X, Lycopodium Clavatum 12X, Methylene Chloride 30X, Methylparaben 30X, Petroselinum Sativum 3X, Phosphoricum Acidum 12X, Propylparaben 30X, Selenium Metallicum 12X, Sodium Benzoate 30X, Sodium Citrate 30X, Taraxacum Officinale 3X, Titanium Dioxide 30X, Zincum Metallicum 12X, Zincum Oxydatum 30X.

PURPOSE:

Arsenicum Album - Muscle Weakness, Aspartame - Headache, Benzalkonium Chloride – Skin Irritation, Beta Vulgaris – Skin Irritation, Bisphenol A – Liver Support, Boldo – Liver Support, Chelidonium Majus – Poor Muscle Coordination, Cobaltum Metallicum – Muscle Weakness, Cuprum Metallicum – Headache, Formalinum - Headache, Glyphosate – Skin Irritation, Iodium – Muscle Weakness, Lycopodium Clavatum – Skin Irritation, Methylene Chloride – Poor Muscle Coordination, Methylparaben – Skin Irritation, Petroselinum Sativum – Skin Irritation, Phosphoricum Acidum – Poor Muscle Coordination, Propylparaben – Liver Support, Selenium Metallicum – Muscle Weakness, Sodium Benzoate - Headache, Sodium Citrate – Skin Irritation, Taraxacum Officinale – Poor Muscle Coordination, Titanium Dioxide – Skin Irritation, Zincum Metallicum - Headache, Zincum Oxydatum – Skin Irritation

USES:

• For the temporary relief of symptoms including:

• headache • liver support • muscle weakness

• skin irritation • poor muscle coordination

These statements are based upon homeopathic principles. They have not been reviewed by the Food and Drug Administration.

WARNINGS:

If pregnant or breastfeeding, ask a health professional before use.

Keep out of reach of children. In case of overdose, contact a physician or Poison Control Center right away.

Tamper Evident: Sealed for your protection. Do not use if seal is broken or missing.

KEEP OUT OF REACH OF CHILDREN:

In case of overdose, contact a physician or Poison Control Center right away.

DIRECTIONS:

1-10 drops under the tongue, 3 times a day or as directed by a health professional. Consult a physician for use in children under 12 years of age.

INACTIVE INGREDIENTS:

Demineralized water, 25% ethanol

QUESTIONS:

Dist. By: Deseret Biologicals, Inc.
469 W. Parkland Drive
Sandy, UT 84070

www.desbio.com

800-827-8204

PACKAGE LABEL DISPLAY:

DesBio

Addiclenz

Homeopathic

NDC 43742-2261-1

1 FL OZ (30 ml)